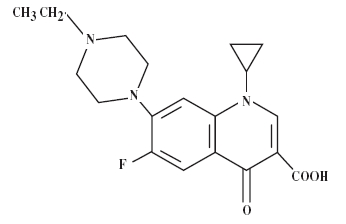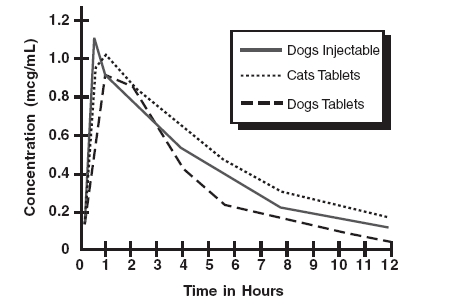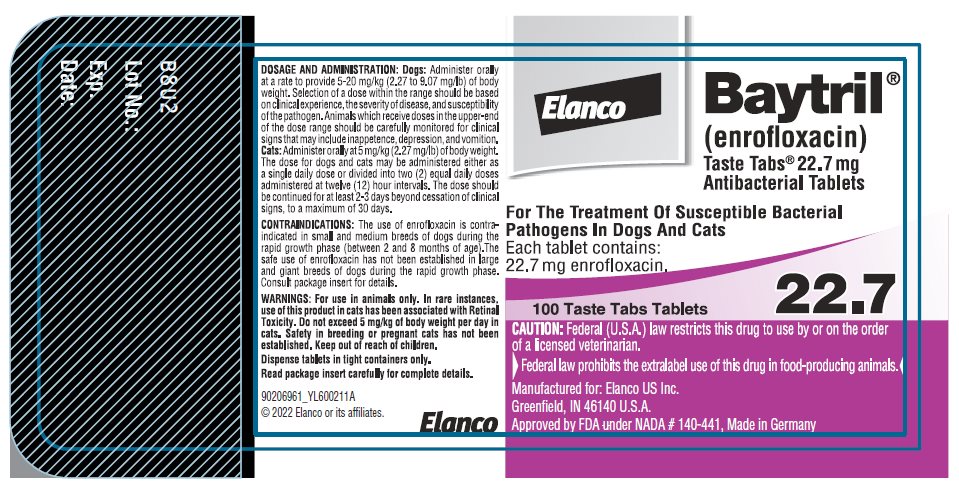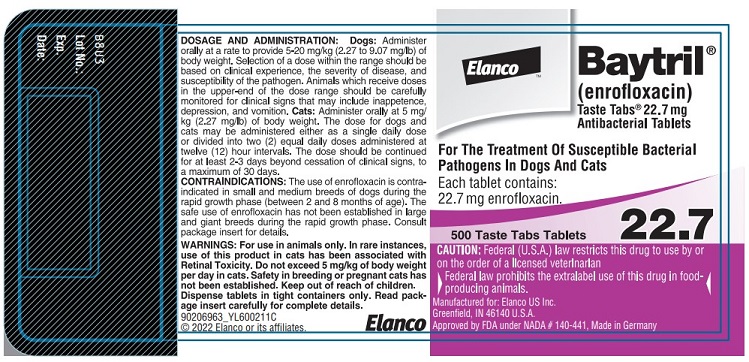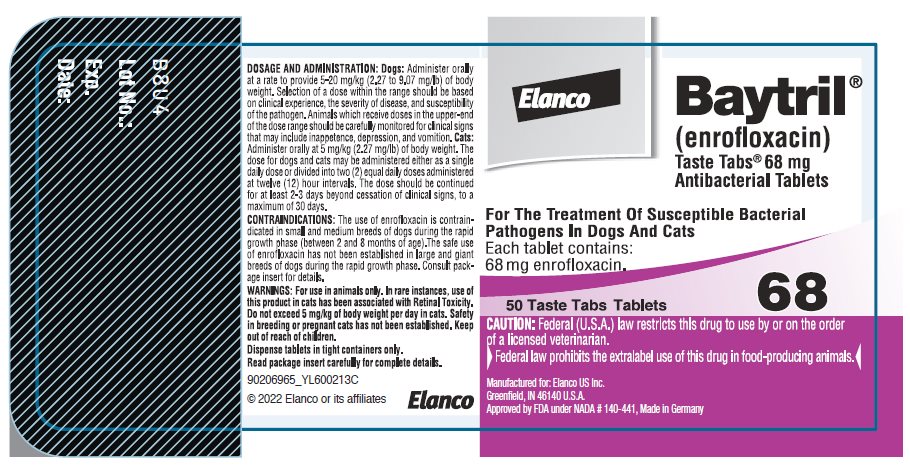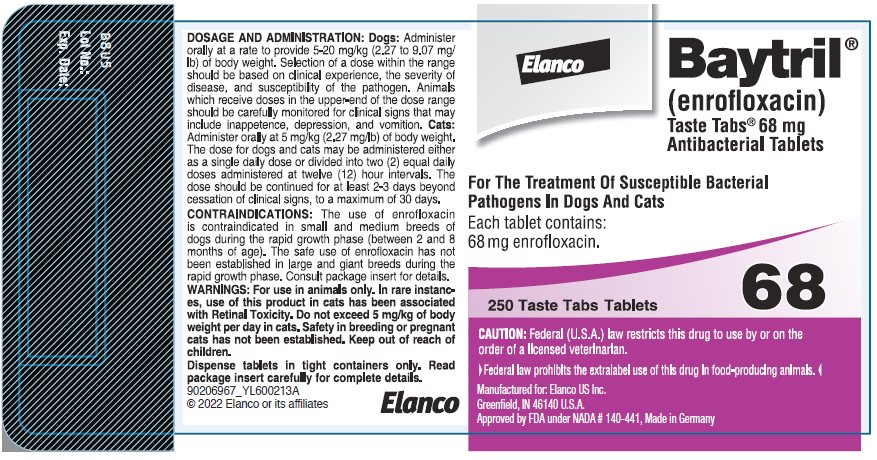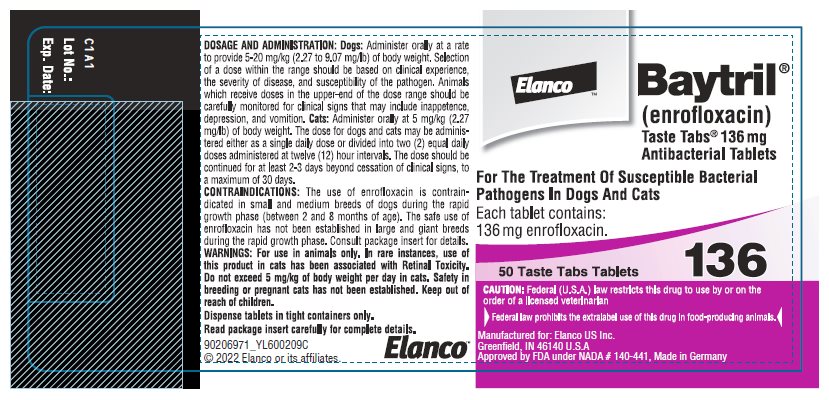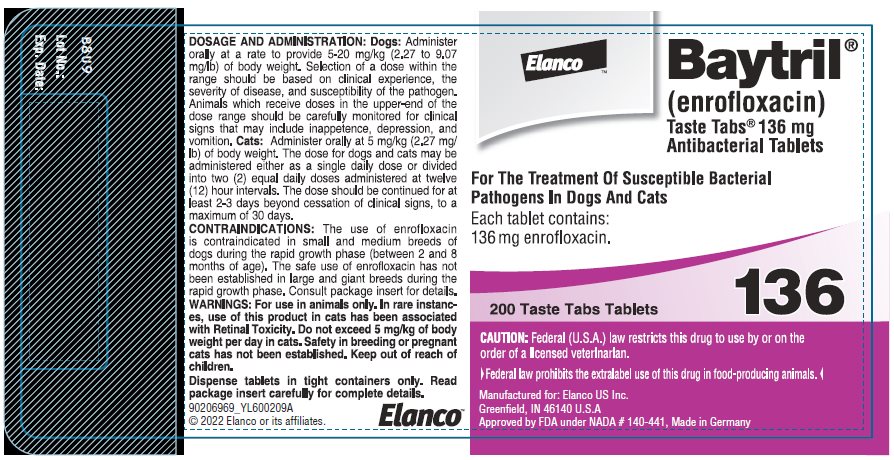 DRUG LABEL: Baytril
NDC: 58198-0024 | Form: TABLET, CHEWABLE
Manufacturer: Elanco US Inc.
Category: animal | Type: PRESCRIPTION ANIMAL DRUG LABEL
Date: 20250124

ACTIVE INGREDIENTS: ENROFLOXACIN 22.7 mg/1 1

Approved by FDA under NADA # 140-441
Elanco Baytril®
(enrofloxacin)
Taste Tabs® 22.7 mg, 68 mg, 136 mg Antibacterial Tablets For Dogs And Cats

CAUTION:

Federal (U.S.A.) law restricts this drug to use by or on the order of a licensed veterinarian.

Federal law prohibits the extralabel use of this drug in food-producing animals.

DESCRIPTION:

Enrofloxacin is a synthetic chemotherapeutic agent from the class of the quinolone carboxylic acid derivatives. It has antibacterial activity against a broad spectrum of Gram negative and Gram positive bacteria (See Tables I and II). It is rapidly absorbed from the digestive tract, penetrating into all measured body tissues and fluids (See Table III). Tablets are available in three sizes (22.7, 68.0 and 136.0 mg enrofloxacin).

CHEMICAL NOMENCLATURE AND STRUCTURAL FORMULA:

1-cyclopropyl-7-(4-ethyl-1-piperazinyl)-6-fluoro-1,4-dihydro-4-oxo-3-quinolinecarboxylic acid.

ACTIONS:

MICROBIOLOGY

Microbiology: Quinolone carboxylic acid derivatives are classified as DNA gyrase inhibitors. The mechanism of action of these compounds is very complex and not yet fully understood. The site of action is bacterial gyrase, a synthesis promoting enzyme. The effect on Escherichia coli is the inhibition of DNA synthesis through prevention of DNA supercoiling. Among other things, such compounds lead to the cessation of cell respiration and division. They may also interrupt bacterial membrane integrity.^1

Enrofloxacin is bactericidal, with activity against both Gram negative and Gram positive bacteria. The minimum inhibitory concentrations (MICs) were determined for a series of 39 isolates representing 9 genera of bacteria from natural infections in dogs and cats, selected principally because of resistance to one or more of the following antibiotics: ampicillin, cephalothin, colistin, chloramphenicol, erythromycin, gentamicin, kanamycin, penicillin, streptomycin, tetracycline, triple sulfa and sulfa/trimethoprim. The MIC values for enrofloxacin against these isolates are presented in Table I. Most strains of these organisms were found to be susceptible to enrofloxacin in vitro but the clinical significance has not been determined for some of the isolates.

The susceptibility of organisms to enrofloxacin should be determined using enrofloxacin 5 mcg disks. Specimens for susceptibility testing should be collected prior to the initiation of enrofloxacin therapy.

TABLE I — MIC Values for Enrofloxacin Against Canine and Feline Pathogens (Diagnostic laboratory isolates, 1984)
Organisms | Isolates | MIC Range (mcg/mL)
Bacteroides spp. | 2 | 2
Bordetella bronchiseptica | 3 | 0.125-0.5
Brucella canis | 2 | 0.125-0.25
Clostridium perfringens | 1 | 0.5
Escherichia coli | 5 [Includes feline isolates.] | ≤0.016-0.031
Klebsiella spp. | 11 | 0.031-0.5
Proteus mirabilis | 6 | 0.062-0.125
Pseudomonas aeruginosa | 4 | 0.5-8
Staphylococcus spp. | 5 | 0.125

The inhibitory activity on 120 isolates of seven canine urinary pathogens was also investigated and is listed in Table II.

TABLE II — MIC Values for Enrofloxacin Against Canine Urinary Pathogens (Diagnostic laboratory isolates, 1985)
Organisms | Isolates | MIC Range (mcg/mL)
E. coli | 30 | 0.06-2.0
P. mirabilis | 20 | 0.125-2.0
K. pneumoniae | 20 | 0.06-0.5
P. aeruginosa | 10 | 1.0-8.0
Enterobacter spp. | 10 | 0.06-1.0
Staph. (coag. +) | 20 | 0.125-0.5
Strep. (alpha hemol.) | 10 | 0.5-8.0

Distribution in the Body: Enrofloxacin penetrates into all canine and feline tissues and body fluids. Concentrations of drug equal to or greater than the MIC for many pathogens (See Tables I, II and III) are reached in most tissues by two hours after dosing at 2.5 mg/kg and are maintained for 8-12 hours after dosing. Particularly high levels of enrofloxacin are found in urine. A summary of the body fluid/tissue drug levels at 2 to 12 hours after dosing at 2.5 mg/kg is given in Table III.

TABLE III — Body Fluid/Tissue distribution of Enrofloxacin in Dogs and Cats
 | Single Oral Dose = 2.5 mg/kg (1.13 mg/lb)
 | Post-treatment Enrofloxacin Levels
 | Canine (n = 2) |  | Feline (n = 4)
Body Fluids (mcg/mL) | 2 Hr. | 8 Hr. | 2 Hr. | 12 Hr.
Bile | – | – | 2.13 | 1.97
Cerebrospinal Fluid | – | – | 0.37 | 0.10
Urine | 43.05 | 55.35 | 12.81 | 26.41
Eye Fluids | 0.53 | 0.66 | 0.45 | 0.65
Whole Blood | 1.01 | 0.36 | – | –
Plasma | 0.67 | 0.33 | – | –
Serum | – | – | 0.48 | 0.18
Tissues (mcg/g) Hematopoietic System
Liver | 3.02 | 1.36 | 1.84 | 0.37
Spleen | 1.45 | 0.85 | 1.33 | 0.52
Bone Marrow | 2.10 | 1.22 | 1.68 | 0.64
Lymph Node | 1.32 | 0.91 | 0.49 | 0.21
Urogenital System
Kidney | 1.87 | 0.99 | 1.43 | 0.37
Bladder Wall | 1.36 | 0.98 | 1.16 | 0.55
Testes | 1.36 | 1.10 | 1.01 | 0.28
Prostate | 1.36 | 2.20 | 1.88 | 0.55
Ovaries | – | – | 0.78 | 0.56
Uterine Wall | 1.59 | 0.29 | 0.81 | 1.05
Gastrointestinal and Cardiopulmonary Systems
Lung | 1.34 | 0.82 | 0.91 | 0.33
Heart | 1.88 | 0.78 | 0.84 | 0.32
Stomach | 3.24 | 2.16 | 3.26 | 0.27
Small Intestine | 2.10 | 1.11 | 2.72 | 0.40
Large Intestine | – | – | 0.94 | 1.10
Other
Fat | 0.52 | 0.40 | 0.24 | 0.11
Skin | 0.66 | 0.48 | 0.46 | 0.17
Muscle | 1.62 | 0.77 | 0.53 | 0.29
Brain | 0.25 | 0.24 | 0.22 | 0.12
Mammary Gland | 0.45 | 0.21 | 0.36 | 0.30
Feces | 1.65 | 9.97 | 0.37 | 4.18

PHARMACOKINETICS

Pharmacokinetics: In dogs, the absorption and elimination characteristics of the oral formulation are linear (plasma concentrations increase proportionally with dose) when enrofloxacin is administered at up to 11.5 mg/kg, twice daily.^2 Approximately 80% of the orally administered dose enters the systemic circulation unchanged. The eliminating organs, based on the drug’s body clearance time, can readily remove the drug with no indication that the eliminating mechanisms are saturated. The primary route of excretion is via the urine. The absorption and elimination characteristics beyond this point are unknown. In cats, no oral absorption information is available at other than 2.5 mg/kg, administered orally as a single dose. Saturable absorption and/or elimination processes may occur at greater doses. When saturation of the absorption process occurs, the plasma concentration of the active moiety will be less than predicted, based on the concept of dose proportionality.

Following an oral dose in dogs of 2.5 mg/kg (1.13 mg/lb), enrofloxacin reached 50% of its maximum serum concentration in 15 minutes and peak serum level was reached in one hour. The elimination half-life in dogs is approximately 2^1/2-3 hours at that dose, while in cats it is greater than 4 hours. In a study comparing dogs and cats, the peak concentration and the time to peak concentration were not different.

A graph indicating the mean serum levels following a dose of 2.5 mg/kg (1.13 mg/lb) in dogs (oral and intramuscular) and cats (oral) is shown in Figure 1.

Figure 1- Serum Concentrations of Enrofloxacin Following a Single Oral or Intramuscular Dose at 2.5 mg/kg in Dogs and a Single Oral Dose at 2.5 mg/kg in Cats.

Breakpoint: Based on pharmacokinetic studies of enrofloxacin in dogs and cats after a single oral administration of 2.5 mg enrofloxacin/kg BW (i.e. half of the lowest-end single daily dose range for dogs and half the single daily dose for cats) and the data listed in Tables I and II, the following breakpoints are recommended for canine and feline isolates.

Zone Diameter (mm) | MIC (μg/mL) | Interpretation
≥ 21 | ≤ 0.5 | Susceptible (S)
18 - 20 | 1 | Intermediate (I)
≤ 17 | ≥ 2 | Resistant (R)

A report of “Susceptible” indicates that the pathogen is likely to be inhibited by generally achievable plasma levels. A report of “Intermediate” is a technical buffer and isolates falling into this category should be retested. Alternatively, the organism may be successfully treated if the infection is in a body site where drug is physiologically concentrated. A report of “Resistant” indicates that the achievable drug concentrations are unlikely to be inhibitory and other therapy should be selected.

Standardized procedures require the use of laboratory control organisms for both standardized disk diffusion assays and standardized dilution assays. The 5 μg enrofloxacin disk should give the following zone diameters and enrofloxacin powder should provide the following MIC values for reference strains.

QC strain | MIC (μg/mL) | Zone Diameter (mm)
E. coli ATCC 25922 | 0.008 - 0.03 | 32 - 40
P. aeruginosa ATCC 27853 | 1 - 4 | 15 - 19
S. aureus ATCC 25923 |  | 27 - 31
S. aureus ATCC 29213 | 0.03 - 0.12

INDICATIONS:

Baytril (brand of enrofloxacin) Taste Tabs Antibacterial Tablets are indicated for the management of diseases associated with bacteria susceptible to enrofloxacin. Baytril Antibacterial Tablets are indicated for use in dogs and cats.

EFFICACY CONFIRMATION:

Dogs: Clinical efficacy was established in dermal infections (wounds and abscesses) associated with susceptible strains of Escherichia coli, Klebsiella pneumoniae, Proteus mirabilis, and Staphylococcus intermedius; respiratory infections (pneumonia, tonsillitis, rhinitis) associated with susceptible strains of Escherichia coli and Staphylococcus aureus; and urinary cystitis associated with susceptible strains of Escherichia coli, Proteus mirabilis, and Staphylococcus aureus.

Palatability: Free choice palatability in dogs was confirmed in a study in which 350 individual dosings resulted in a voluntary ingestion rate of 73%.

Cats: Clinical efficacy was established in dermal infections (wounds and abscesses) associated with susceptible strains of Pasteurella multocida, Staphylococcus aureus, and Staphylococcus epidermidis.

CONTRAINDICATIONS:

Enrofloxacin is contraindicated in dogs and cats known to be hypersensitive to quinolones.

Dogs: Based on the studies discussed under the section on Animal Safety Summary, the use of enrofloxacin is contraindicated in small and medium breeds of dogs during the rapid growth phase (between 2 and 8 months of age). The safe use of enrofloxacin has not been established in large and giant breeds during the rapid growth phase. Large breeds may be in this phase for up to one year of age and the giant breeds for up to 18 months. In clinical field trials utilizing a daily oral dose of 5.0 mg/kg, there were no reports of lameness or joint problems in any breed. However, controlled studies with histological examination of the articular cartilage have not been conducted in the large or giant breeds.

ADVERSE REACTIONS:

Dogs: Two of the 270 (0.7%) dogs treated with Baytril (brand of enrofloxacin) Tablets at 5.0 mg/kg per day in the clinical field studies exhibited side effects, which were apparently drug-related. These two cases of vomition were self-limiting.

Post-Approval Experience: The following adverse experiences, although rare, are based on voluntary post-approval adverse drug experience reporting. The categories of reactions are listed in decreasing order of frequency by body system.

Gastrointestinal: anorexia, diarrhea, vomiting, elevated liver enzymes

Neurologic: ataxia, seizures

Behavioral: depression, lethargy, nervousness

Cats: No drug-related side effects were reported in 124 cats treated with Baytril (brand of enrofloxacin) Tablets at 5.0 mg/kg per day for 10 days in clinical field studies.

Post-Approval Experience: The following adverse experiences, although rare, are based on voluntary post-approval adverse drug experience reporting. The categories of reactions are listed in decreasing order of frequency by body system.

Ocular: Mydriasis, retinal degeneration (retinal atrophy, attenuated retinal vessels, and hyperreflective tapeta have been reported), loss of vision. Mydriasis may be an indication of impending or existing retinal changes.

Gastrointestinal: vomiting, anorexia, elevated liver enzymes, diarrhea

Neurologic: ataxia, seizures

Behavioral: depression, lethargy, vocalization, aggression

To report adverse reactions, call 888-545-5973.
For additional information about reporting adverse drug experiences for animal drugs, contact FDA at 1-888-FDA-VETS or https://www.fda.gov/reportanimalae.

ANIMAL SAFETY SUMMARY:

Dogs: Adult dogs receiving enrofloxacin orally at a daily dosage rate of 52 mg/kg for 13 weeks had only isolated incidences of vomition and inappetence. Adult dogs receiving the tablet formulation for 30 consecutive days at a daily treatment of 25 mg/kg did not exhibit significant clinical signs nor were there effects upon the clinical chemistry, hematological or histological parameters. Daily doses of 125 mg/kg for up to 11 days induced vomition, inappetence, depression, difficult locomotion and death while adult dogs receiving 50 mg/kg/day for 14 days had clinical signs of vomition and inappetence.

Adult dogs dosed intramuscularly for three treatments at 12.5 mg/kg followed by 57 oral treatments at 12.5 mg/kg, all at 12 hour intervals, did not exhibit either significant clinical signs or effects upon the clinical chemistry, hematological or histological parameters.

Oral treatment of 15 to 28 week old growing puppies with daily dosage rates of 25 mg/kg has induced abnormal carriage of the carpal joint and weakness in the hindquarters. Significant improvement of clinical signs is observed following drug withdrawal. Microscopic studies have identified lesions of the articular cartilage following 30 day treatments at either 5, 15 or 25 mg/kg in this age group. Clinical signs of difficult ambulation or associated cartilage lesions have not been observed in 29 to 34 week old puppies following daily treatments of 25 mg/kg for 30 consecutive days nor in 2 week old puppies with the same treatment schedule.

Tests indicated no effect on circulating microfilariae or adult heartworms (Dirofilaria immitis) when dogs were treated at a daily dosage rate of 15 mg/kg for 30 days. No effect on cholinesterase values was observed.

No adverse effects were observed on reproductive parameters when male dogs received 10 consecutive daily treatments of 15 mg/kg/day at 3 intervals (90, 45 and 14 days) prior to breeding or when female dogs received 10 consecutive daily treatments of 15 mg/kg/day at 4 intervals: between 30 and 0 days prior to breeding, early pregnancy (between 10th & 30th days), late pregnancy (between 40th & 60th days), and during lactation (the first 28 days).

Cats: Cats in age ranges of 3 to 4 months and 7 to 10 months received daily treatments of 25 mg/kg for 30 consecutive days with no adverse effects upon the clinical chemistry, hematological or histological parameters. In cats 7-10 months of age treated daily for 30 consecutive days, 2 of 4 receiving 5 mg/kg, 3 of 4 receiving 15 mg/kg, 2 of 4 receiving 25 mg/kg and 1 of 4 nontreated controls experienced occasional vomition. Five to 7 month old cats had no side effects with daily treatments of 15 mg/kg for 30 days, but 2 of 4 animals had articular cartilage lesions when administered 25 mg/kg per day for 30 days.

Doses of 125 mg/kg for 5 consecutive days to adult cats induced vomition, depression, incoordination and death while those receiving 50 mg/kg for 6 days had clinical signs of vomition, inappetence, incoordination and convulsions, but they returned to normal.

Enrofloxacin was administered to thirty-two (8 per group), six- to eight-month-old cats at doses of 0, 5, 20, and 50 mg/kg of body weight once a day for 21 consecutive days. There were no adverse effects observed in cats that received 5 mg/kg body weight of enrofloxacin. The administration of enrofloxacin at 20 mg/kg body weight or greater caused salivation, vomition, and depression. Additionally, dosing at 20 mg/kg body weight or greater resulted in mild to severe fundic lesions on ophthalmologic examination (change in color of the fundus, central or generalized retinal degeneration), abnormal electroretinograms (including blindness), and diffuse light microscopic changes in the retina.

DRUG INTERACTIONS:

Compounds that contain metal cations (e.g., aluminum, calcium, iron, magnesium) may reduce the absorption of some quinolone-class drugs from the intestinal tract. Concomitant therapy with other drugs that are metabolized in the liver may reduce the clearance rates of the quinolone and the other drug.

Dogs: Enrofloxacin has been administered to dogs at a daily dosage rate of 10 mg/kg concurrently with a wide variety of other health products including anthelmintics (praziquantel, febantel, sodium disophenol), insecticides (fenthion, pyrethrins), heartworm preventatives (diethylcarbamazine) and other antibiotics (ampicillin, gentamicin sulfate, penicillin, dihydrostreptomycin). No incompatibilities with other drugs are known at this time.

Cats: Enrofloxacin was administered at a daily dosage rate of 5 mg/kg concurrently with anthelmintics (praziquantel, febantel), an insecticide (propoxur) and another antibacterial (ampicillin). No incompatibilities with other drugs are known at this time.

WARNINGS:

For use in animals only. In rare instances, use of this product in cats has been associated with Retinal Toxicity. Do not exceed 5 mg/kg of body weight per day in cats. Safety in breeding or pregnant cats has not been established. Keep out of reach of children.

Avoid contact with eyes. In case of contact, immediately flush eyes with copious amounts of water for 15 minutes. In case of dermal contact, wash skin with soap and water. Consult a physician if irritation persists following ocular or dermal exposure. Individuals with a history of hypersensitivity to quinolones should avoid this product. In humans, there is a risk of user photosensitization within a few hours after excessive exposure to quinolones. If excessive accidental exposure occurs, avoid direct sunlight.

For customer service or to obtain product information, including Safety Data Sheet, call 888-545-5973.

PRECAUTIONS:

Quinolone-class drugs should be used with caution in animals with known or suspected Central Nervous System (CNS) disorders. In such animals, quinolones have, in rare instances, been associated with CNS stimulation which may lead to convulsive seizures.

Quinolone-class drugs have been associated with cartilage erosions in weight-bearing joints and other forms of arthropathy in immature animals of various species.

The use of fluoroquinolones in cats has been reported to adversely affect the retina. Such products should be used with caution in cats.

DOSAGE AND ADMINISTRATION:

Dogs: Administer orally at a rate to provide 5-20 mg/kg (2.27 to 9.07 mg/lb) of body weight. Selection of a dose within the range should be based on clinical experience, the severity of disease, and susceptibility of the pathogen. Animals which receive doses in the upper-end of the dose range should be carefully monitored for clinical signs that may include inappetence, depression, and vomition.

Weight of Dog | Once Daily Dosing Chart
 | 5.0 mg/kg | 10.0 mg/kg | 15.0 mg/kg | 20.0 mg/kg
9.1 kg (20 lb) | 2 x 22.7 mg tablets | 1 x 22.7 mg plus 1 x 68 mg tablets | 1 x 136 mg tablet | 1 x 136 mg plus 2 x 22.7 mg tablets
27.2 kg (60 lb) | 1 x 136 mg tablet | 2 x 136 mg tablets | 3 x 136 mg tablets | 4 x 136 mg tablets
All tablet sizes are double scored for accurate dosing.

Cats: Administer orally at 5 mg/kg (2.27 mg/lb) of body weight. The dose for dogs and cats may be administered either as a single daily dose or divided into two (2) equal daily doses administered at twelve (12) hour intervals. The dose should be continued for at least 2-3 days beyond cessation of clinical signs, to a maximum of 30 days.

Weight of Cat | Once Daily Dosing Chart (5 mg/kg/day)
5 lb (2.27 kg) | 1/2 x 22.7 mg tablet
10 lb (4.5 kg) | 1 x 22.7 mg tablet
15 lb (6.8 kg) | 1 and 1/2 x 22.7 mg tablets or 1/2 x 68 mg tablet
All tablet sizes are double scored for accurate dosing.

Palatability: Most dogs will consume Baytril Taste Tabs Tablets willingly when offered by hand. Alternatively the tablet(s) may be offered in food or hand-administered (pilled) as with other oral tablet medications. In cats, Baytril Taste Tabs Tablets should be pilled. After administration, watch the animal closely to be certain the entire dose has been consumed.

Dogs & Cats: The duration of treatment should be selected based on clinical evidence. Generally, administration of Baytril Tablets should continue for at least 2-3 days beyond cessation of clinical signs. For severe and/or complicated infections, more prolonged therapy, up to 30 days, may be required. If no improvement is seen within five days, the diagnosis should be reevaluated and a different course of therapy considered.

The lower limit of the dose range in dogs and the daily dose for cats was based on efficacy studies in dogs and cats where enrofloxacin was administered at 2.5 mg/kg twice daily. Target animal safety and toxicology were used to establish the upper limit of the dose range for dogs and treatment duration for dogs and cats.

STORAGE:

Dispense tablets in tight containers only. Baytril Taste Tablets should be stored at or below 77° F (25° C).

HOW SUPPLIED:

Baytril Tablets Tablet Size | Tablets/Bottle
22.7 mg | 100 Double Scored
22.7 mg | 500 Double Scored
68.0 mg | 50 Double Scored
68.0 mg | 250 Double Scored
136.0 mg | 50 Double Scored
136.0 mg | 200 Double Scored

REFERENCES:

1 Doughherty, T.J., & Saukkonen, J.J. (1985). Membrane permeability changes associated with DNA gyrase inhibitors in Escherichia Coli. Antimicrob Agents Chemother, 28 (2), 200-206.
2 Walker, R.D., Stein, G.E., Hauptmam, J.G., McDonald, K.H. (1992). Pharmacokinetic evaluation of enrofloxacin administered orally to healthy dogs. Am J Vet Res, 53 (12):2315-2319.

Manufactured for: Elanco US Inc.
Greenfield, IN 46140 U.S.A.

Made in Germany
90206961_YL600211A
90206963_YL600211C
90206967_YL600213A
90206965_YL600213C
90206969_YL600209A
90206971_YL600209C

Baytril is sold by Elanco or its affiliates and is not a product of Bayer. The product name Baytril is owned by Bayer and used under license.
Taste Tabs, Elanco and the diagonal bar logo are trademarks of Elanco or its affiliates.

©2022 Elanco or its affiliates.

Elanco

Approved by FDA under NADA # 140-441
Revised: January 2022

Principal Display Panel – 22.7 mg Bottle Label

Elanco

Baytril®
(enrofloxacin)
Taste Tabs® 22.7 mg
Antibacterial Tablets

For The Treatment Of Susceptible Bacterial
Pathogens In Dogs And Cats

Each tablet contains:
22.7 mg enrofloxacin.

100 Taste Tabs Tablets

22.7

CAUTION: Federal (U.S.A.) law restricts this drug to use by or on the order
of a licensed veterinarian.

Federal law prohibits the extralabel use of this drug in food-producing animals.

Manufactured for: Elanco US Inc.
Greenfield, IN 46140 U.S.A.
Approved by FDA under NADA # 140-441, Made in Germany

ElancoTM

Baytril®
(enrofloxacin)
Taste Tabs® 22.7 mg
Antibacterial Tablets

For The Treatment Of Susceptible Bacterial
Pathogens In Dogs And Cats

Each tablet contains:
22.7 mg enrofloxacin.

500 Taste Tabs Tablets

22.7

CAUTION: Federal (U.S.A.) law restricts this drug to use by or
on the order of a licensed veterinarian.

Federal law prohibits the extralabel use of this drug in food-
producing animals.

Manufactured for: Elanco US Inc.
Greenfield, IN 46140 U.S.A.
Approved by FDA under NADA # 140-441, Made in Germany

Principal Display Panel - 68 mg Bottle Label

Elanco

Baytril®
(enrofloxacin)
Taste Tabs® 68 mg
Antibacterial Tablets

For The Treatment Of Susceptible Bacterial
Pathogens In Dogs And Cats

Each tablet contains:
68 mg enrofloxacin.

50 Taste Tabs Tablets

68

CAUTION: Federal (U.S.A.) law restricts this drug to use by or on the order
of a licensed veterinarian.

Federal law prohibits the extralabel use of this drug in food-producing animals.

Manufactured for: Elanco US Inc.
Greenfield, IN 46140 U.S.A.
Approved by FDA under NADA # 140-441, Made in Germany

Elanco

Baytril®
(enrofloxacin)
Taste Tabs® 68 mg
Antibacterial Tablets

For The Treatment Of Susceptible Bacterial
Pathogens In Dogs And Cats

Each tablet contains:
68 mg enrofloxacin.

250 Taste Tabs Tablets

68

CAUTION: Federal (U.S.A.) law restricts this drug to use by or on the
order of a licensed veterinarian.

Federal law prohibits the extralabel use of this drug in food-producing animals.

Manufactured for: Elanco US Inc.
Greenfield, IN 46140 U.S.A.
Approved by FDA under NADA # 140-441, Made in Germany

Principal Display Panel – 136 mg Bottle Label

ElancoTM

Baytril®
(enrofloxacin)
Taste Tabs® 136 mg
Antibacterial Tablets

For The Treatment Of Susceptible Bacterial
Pathogens In Dogs And Cats

Each tablet contains:
136 mg enrofloxacin.

50 Taste Tabs Tablets

136

CAUTION: Federal (U.S.A.) law restricts this drug to use by or on the
order of a licensed veterinarian.

Federal law prohibits the extralabel use of this drug in food-producing animals.

Manufactured for: Elanco US Inc.
Greenfield, IN 46140 U.S.A
Approved by FDA under NADA # 140-441, Made in Germany

ElancoTM

Baytril®
(enrofloxacin)
Taste Tabs® 136 mg
Antibacterial Tablets

For The Treatment Of Susceptible Bacterial
Pathogens In Dogs And Cats

Each tablet contains:
136 mg enrofloxacin.

200 Taste Tabs Tablets

136

CAUTION: Federal (U.S.A.) law restricts this drug to use by or on the
order of a licensed veterinarian.

Federal law prohibits the extralabel use of this drug in food-producing animals.

Manufactured for: Elanco US Inc.
Greenfield, IN 46140 U.S.A
Approved by FDA under NADA # 140-441, Made in Germany